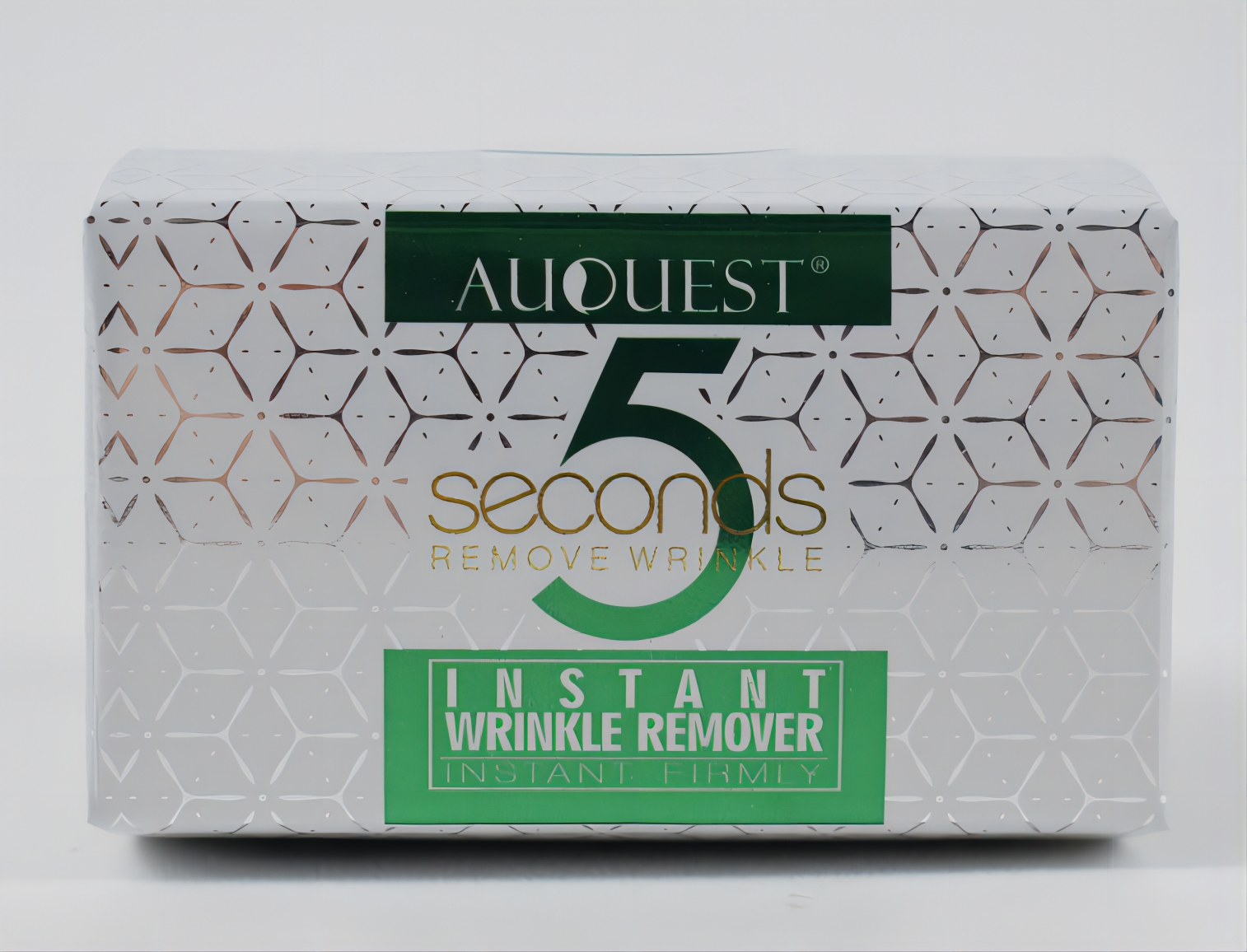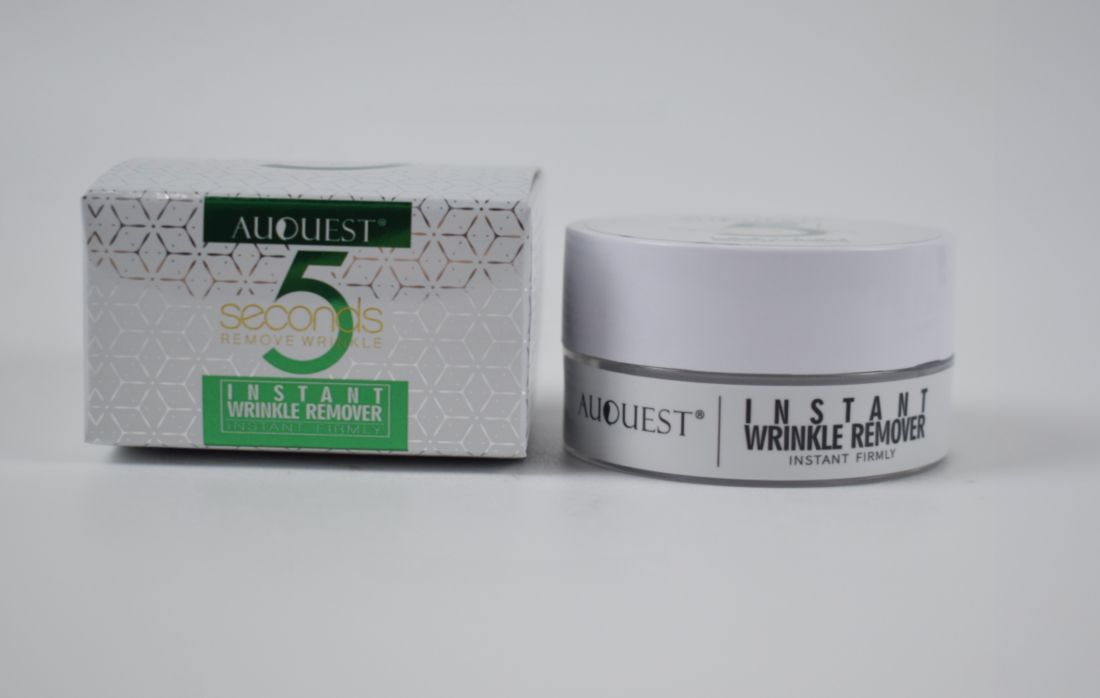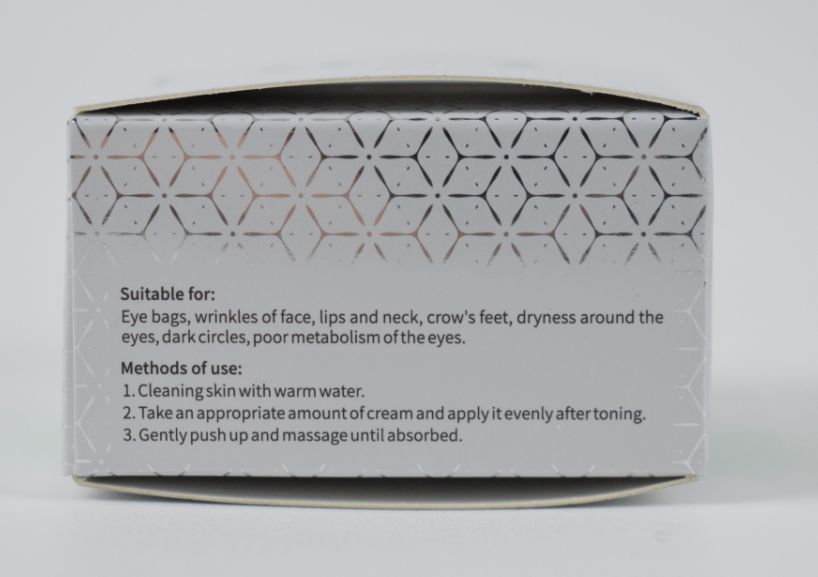 DRUG LABEL: AUQUEST  INSTANT WRINKLE REMOVER
NDC: 83675-032 | Form: CREAM
Manufacturer: Guangzhou Hanhai Trading Co., Ltd
Category: otc | Type: HUMAN OTC DRUG LABEL
Date: 20231210

ACTIVE INGREDIENTS: HYDROGENATED JOJOBA OIL 5 mg/100 g; HOUTTUYNINE 2.5 mg/100 g; PEPTIDE-T 81.7 g/100 g; BOMBYX MORI FIBER 3 mg/100 g
INACTIVE INGREDIENTS: HYDROLYZED BOVINE ELASTIN (BASE; 1000 MW); MYRRH; LUPANINE DIHYDROCHLORIDE, (+/-)-; WITCH HAZEL

Active Ingredient

Hydration twenty-one peptide, Pure natural fish carp active crystallinehydrate, Silk peptide, Houttuyniaanti-wrinkle factor

Purpose

remove wrinkles

Use

1.Cleaning skin with warm water.
2.Take an appropriate amount of cream and apply it evenly after toning.
3.Gently push up and massage until absorbed.

Warnings

1.For sensitive skin, it is recommended to conduct an allergy test on the back of the ear before using the product. Useit if no adverse effects occur.
2.lf such abnormalities as rash, swelling,pruritus or allergic reaction occur during or after applying the product, stop using it immediately and seek medical advice.

Do not use

If discomfort arises, please immediately stop using the product and seek the assistance of a dermatologist.

When Using

In case of sensitive skin, please test the product on the inside of the arm first.
In case of contact with the eyes, rinse immediately with plenty of water.

Stop Use

If discomfort arises, please immediately stop using the product and seek the assistance of a dermatologist.

Ask Doctor

If discomfort arises, please immediately stop using the product and seek the assistance of a dermatologist.

Keep Oot Of Reach Of Children

Directions

1.Cleaning skin with warm water.
2.Take an appropriate amount of cream and apply it evenly after toning.
3.Gently push up and massage until absorbed.

Inactive ingredients

Lupa gum, Myrrh, Azone, Witch hazel Liquid, Hydrolyzed elastin.